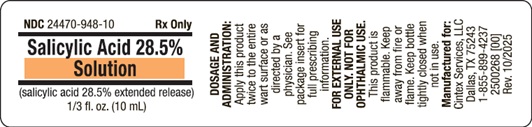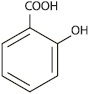 DRUG LABEL: Salicylic Acid
NDC: 24470-948 | Form: SOLUTION
Manufacturer: Cintex Services, LLC
Category: prescription | Type: HUMAN PRESCRIPTION DRUG LABEL
Date: 20251015

ACTIVE INGREDIENTS: SALICYLIC ACID 285 mg/1 mL

Salicylic Acid 28.5% Solution

Salicylic Acid 28.5% Solution (salicylic acid 28.5% extended release)

Rx Only

FOR EXTERNAL USE ONLY. NOT FOR OPHTHALMIC USE.

DESCRIPTION:

Each mL contains 285 mg of salicylic acid extended release in a film-forming virucidal solution consisting of acrylates copolymer, isopropyl alcohol, n-Butyl acetate, polyvinyl butyral, and trimethyl pentanyl diisobutyrate.

The pharmacologic activity of this product is generally attributed to the keratolytic activity of salicylic acid, which is incorporated into a polyacrylic, film-forming virucidal solution designed to cover the wart without the need for a bandage. The structural formula of salicylic acid is:

CLINICAL PHARMACOLOGY:

Although the exact mode of action for salicylic acid in the treatment of warts is unknown, its activity appears to be associated with its keratolytic action, which results in mechanical removal of epidermal cells infected with wart viruses.

INDICATIONS AND USAGE:

This product is indicated for the topical treatment and removal of common warts and plantar warts.

CONTRAINDICATIONS:

This product is contraindicated in persons with known or suspected hypersensitivity to any of the ingredients of the product. Patients with diabetes or impaired blood circulation should not use this product. This product also should not be used on moles, birthmarks, and unusual warts with hair growing from them, or warts on the face.

WARNINGS: KEEP OUT OF REACH OF CHILDREN.

This product is flammable. Keep away from fire or flame. Keep bottle tightly closed when not in use.

PRECAUTIONS: FOR EXTERNAL USE ONLY. NOT FOR OPHTHALMIC USE.

If contact with eyes or mucous membranes occurs, immediately flush with water for 15 minutes. This product should not be allowed to contact normal skin surrounding the wart site, since localized irritation may occur. Treatment should be discontinued if excessive irritation occurs.

ADVERSE REACTIONS:

Localized irritation may occur if this product is applied to normal skin surrounding the wart; however irritation may normally be controlled by temporarily discontinuing use and by applying the medication only to the wart site when treatment is resumed. To report a serious adverse event, call 1-855-899-4237.

DOSAGE AND ADMINISTRATION:

Prior to applying this product, soak wart in warm water for five minutes. Remove any loose tissue by gently rubbing with a washcloth, emery board, or pumice stone. Dry the wart site thoroughly. Using the brush applicator supplied, apply this product twice to the entire wart surface, allowing the first application to dry before applying the second. Continue treatment once or twice a day or as directed by a physician. Be careful not to apply to surrounding skin.

Clinically visible improvement normally occurs during the first or second week of therapy. Resolution may be expected after four to six weeks of this product’s use, though some warts may take longer to remove.

HOW SUPPLIED:

1/3 fl. oz. (10 mL) bottles, NDC 24470-948-10

Store at 20°C to 25°C (68°F to 77°F), excursions permitted between 15°C to 30°C (between 59°F to 86°F). Brief exposure to temperatures up to 40°C (104°F) may be tolerated provided the mean kinetic temperature does not exceed 25°C (77°F); however, such exposure should be minimized. Protect from freezing and excessive heat. Keep bottle tightly closed.

Manufactured for:
Cintex Services, LLC

Dallas, TX 75243

2500269 [00] Rev. 10/2025